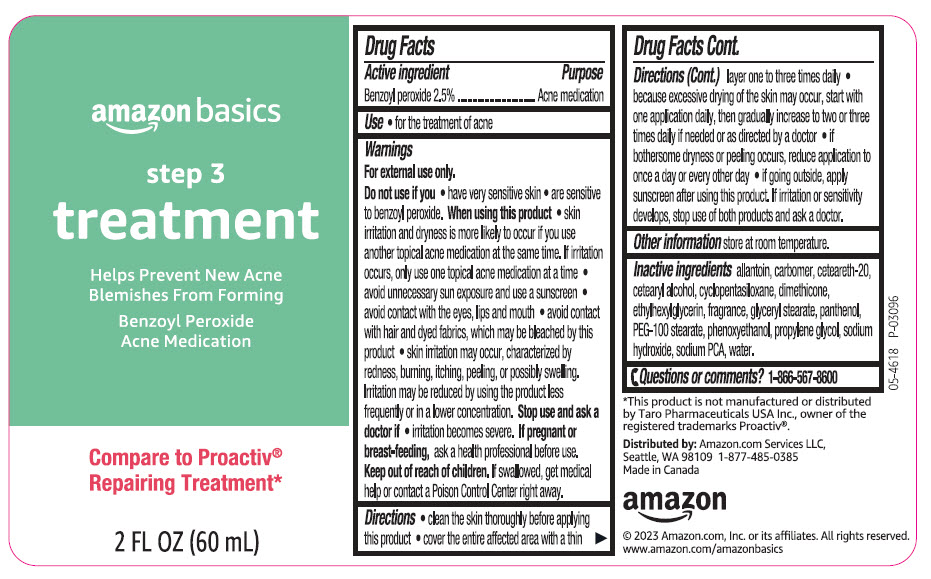 DRUG LABEL: amazon basics step 3 treatment
NDC: 72288-618 | Form: LOTION
Manufacturer: AMAZON.COM SERVICES LLC
Category: otc | Type: HUMAN OTC DRUG LABEL
Date: 20240828

ACTIVE INGREDIENTS: BENZOYL PEROXIDE 25 mg/1 mL
INACTIVE INGREDIENTS: ALLANTOIN; CARBOMER HOMOPOLYMER, UNSPECIFIED TYPE; POLYOXYL 20 CETOSTEARYL ETHER; CETOSTEARYL ALCOHOL; CYCLOMETHICONE 5; Dimethicone; Ethylhexylglycerin; GLYCERYL MONOSTEARATE; Panthenol; PEG-100 Stearate; Phenoxyethanol; Propylene Glycol; Sodium Hydroxide; SODIUM PYRROLIDONE CARBOXYLATE; Water

amazon basics step 3 treatment
Acne medication

Drug Facts

Active ingredient

Benzoyl peroxide 2.5%

Purpose

Acne Medication

Use

for the treatment of acne

Warnings

For external use only

Do not use if you

- have very sensitive skin
- are sensitive to benzoyl peroxide.

When using this product

- skin irritation and dryness is more likely to occur if you use another topical acne medication at the same time. If irritation occurs, only use one topical acne medication at a time.
- avoid unnecessary sun exposure and use a sunscreen
- avoid contact with the eyes, lips, and mouth
- avoid contact with hair and dyed fabrics, which may be bleached by this product
- skin irritation may occur, characterized by redness, burning, itching, peeling, or possibly swelling. Irritation may be reduced by using the product less frequently or in a lower concentration.

Stop use and ask a doctor if

- irritation becomes severe.

PREGNANCY OR BREAST FEEDING

If pregnant or breast-feeding, ask a health professional before use.

Keep out of reach of children. If swallowed, get medical help or contact a Poison Control Center right away.

Directions

- clean the skin thoroughly before applying this product
- cover the entire affected area with a thin layer one to three times daily
- because excessive drying of the skin may occur, start with one application daily, then gradually increase to two or three times daily if needed or as directed by a doctor
- if bothersome dryness or peeling occurs, reduce application to once a day or every other day
- if going outside, apply sunscreen after using this product. If irritation or sensitivity develops, stop use of both products and ask a doctor.

Other information

store at room temperature.

Inactive ingredients

allantoin, carbomer, ceteareth-20, cetearyl alcohol, cyclopentasiloxane, dimethicone, ethylhexylglycerin, fragrance, glyceryl stearate, panthenol, PEG-100 stearate, phenoxyethanol, propylene glycol, sodium hydroxide, sodium PCA, water.

Questions or comments?

1-866-567-8600

Distributed by: Amazon.com Services LLC,
Seattle, WA 98109

PRINCIPAL DISPLAY PANEL - 60 mL Bottle Label

amazon basics

step 3
treatment

Helps Prevent New Acne
Blemishes From Forming

Benzoyl Peroxide
Acne Medication

Compare to Proactiv®
Repairing Treatment*

2 FL OZ (60 mL)